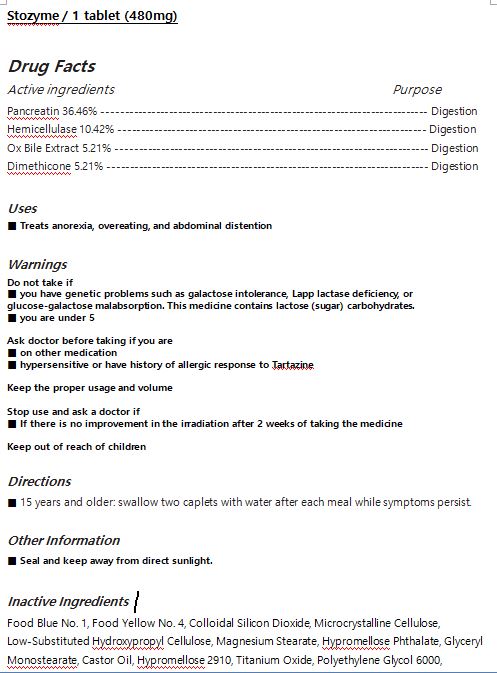 DRUG LABEL: Stozyme
NDC: 72850-0004 | Form: TABLET
Manufacturer: Chunwoo Pharmaceutical Co., Ltd.
Category: otc | Type: HUMAN OTC DRUG LABEL
Date: 20191104

ACTIVE INGREDIENTS: HEMICELLULASE (ASPERGILLUS NIGER) 10.42 1/100 1; DIMETHICONE 5.21 1/100 1; PANCRELIPASE 36.46 1/100 1; BOS TAURUS BILE 5.21 1/100 1
INACTIVE INGREDIENTS: POLYETHYLENE GLYCOL 6000

ACTIVE INGREDIENT

Pancreatin 36.46%

Hemicellulase 10.42%

Ox Bile Extract 5.21%

Dimethicone 5.21%

INACTIVE INGREDIENT

Food Blue No. 1, Food Yellow No. 4, Colloidal Silicon Dioxide, Microcrystalline Cellulose, Low-Substituted Hydroxypropyl Cellulose, Magnesium Stearate, Hypromellose Phthalate, Glyceryl Monostearate, Castor Oil, Hypromellose 2910, Titanium Oxide, Polyethylene Glycol 6000,

PURPOSE

Anorexia, overeating, and abdominal distention

KEEP OUT OF REACH OF CHILDREN

WARNING

Do not take if

-you have genetic problems such as galactose intolerance, Lapp lactase deficiency, or glucose-galactose malabsorption. This medicine contains lactose (sugar) carbohydrates.

-you are under 5

Ask doctor before taking if

- you are on other medication

- you are hypersensitive or have history of allergic response to Tartazine

Keep the proper usage and volume

Stop use and ask a doctor if

- If there is no improvement in the irradiation after 2 weeks of taking the medicine

USES

for oral use only

INDICATION & USAGE SECTION

Treats anorexia, overeating, and abdominal distention